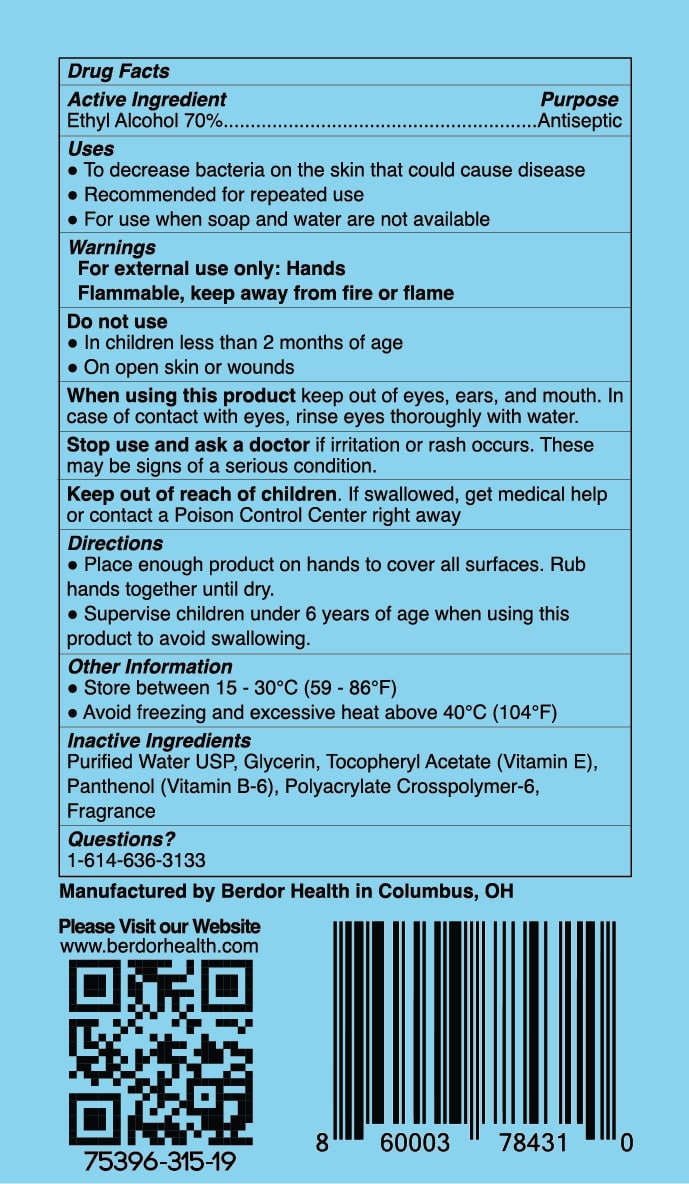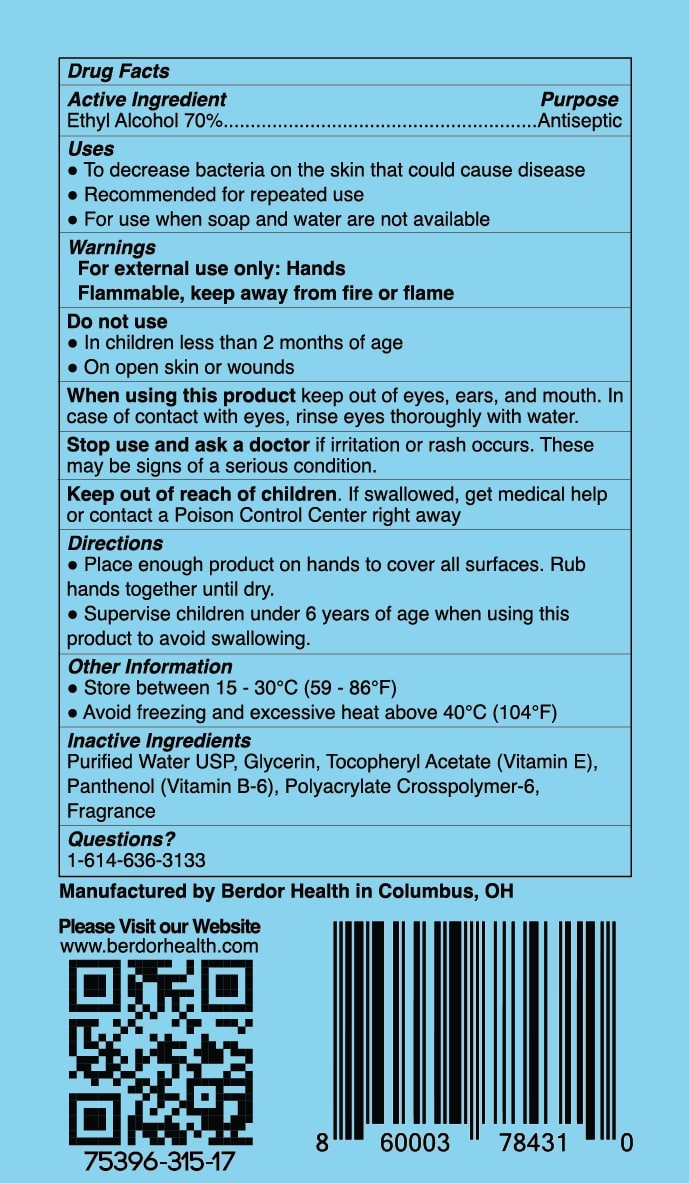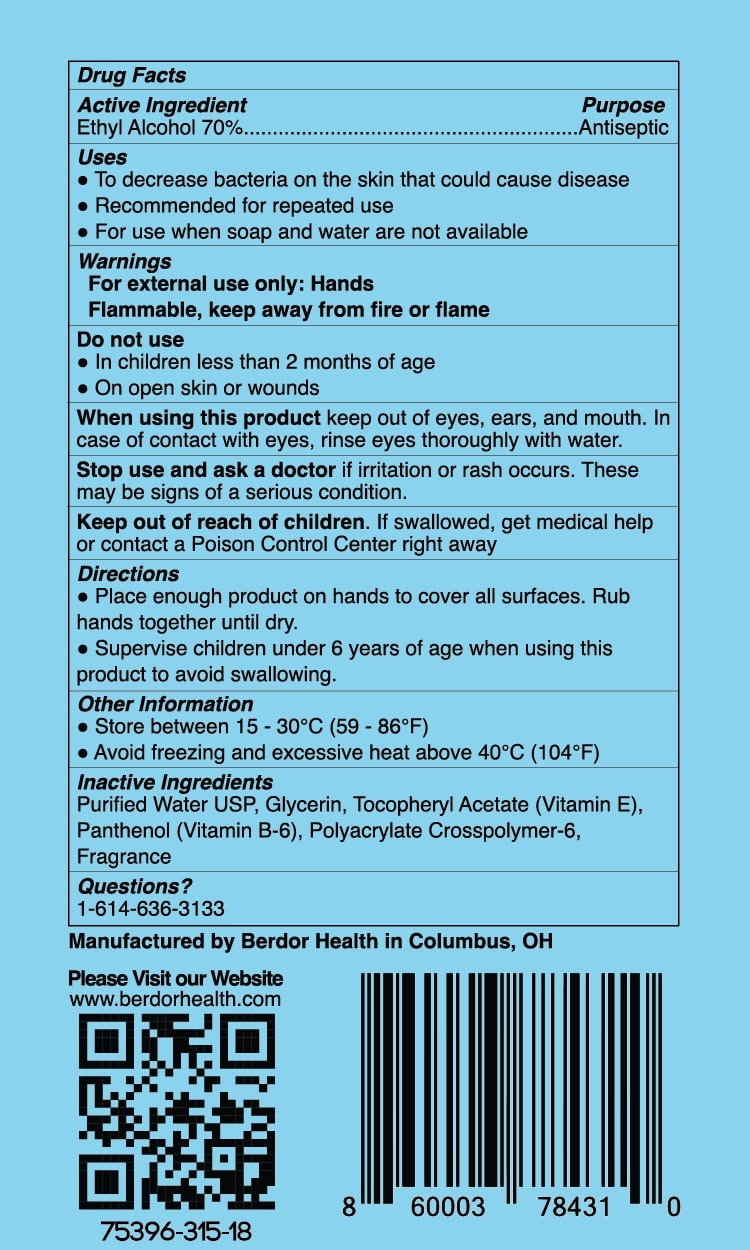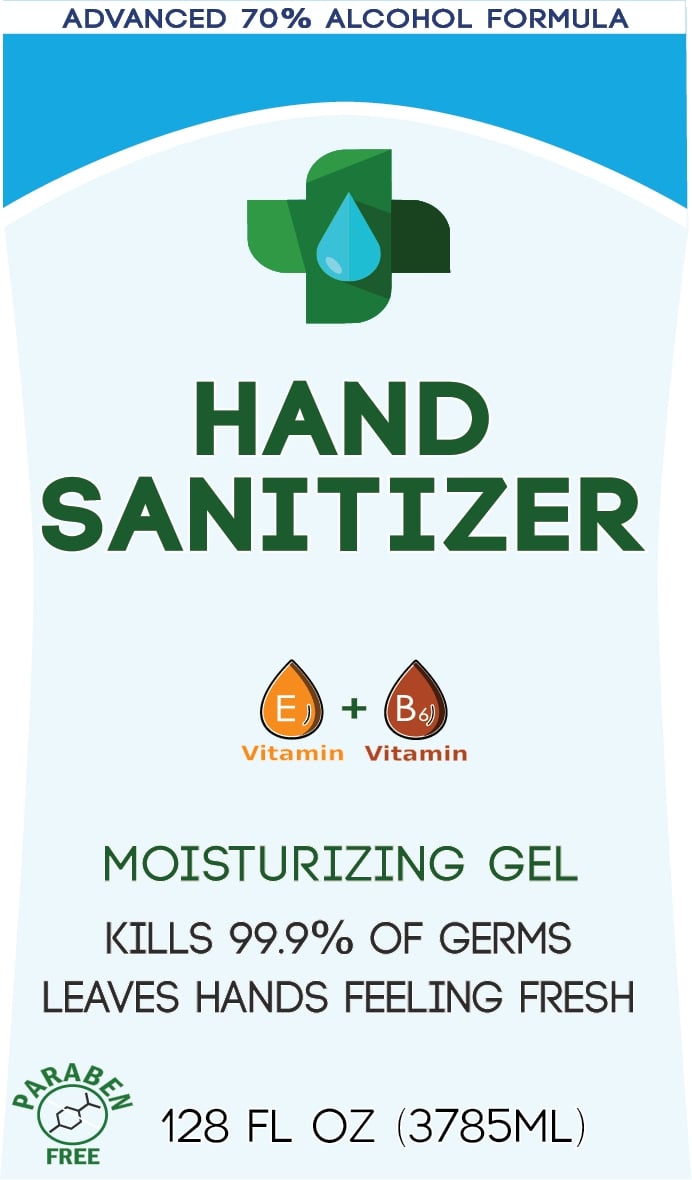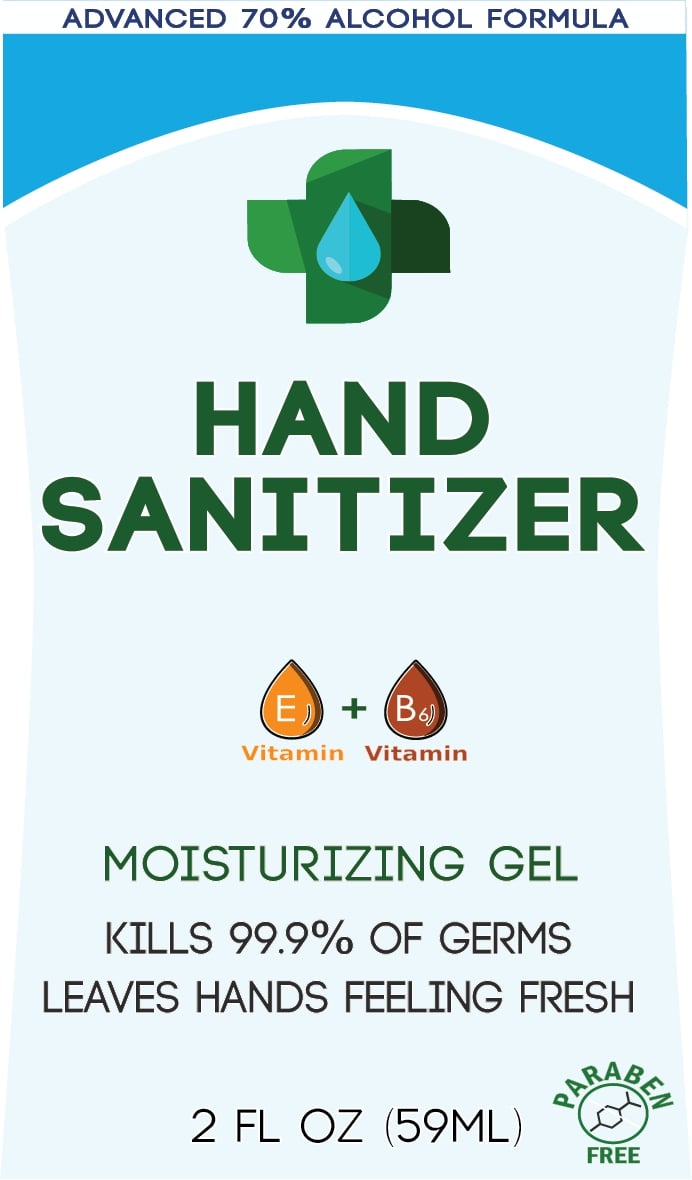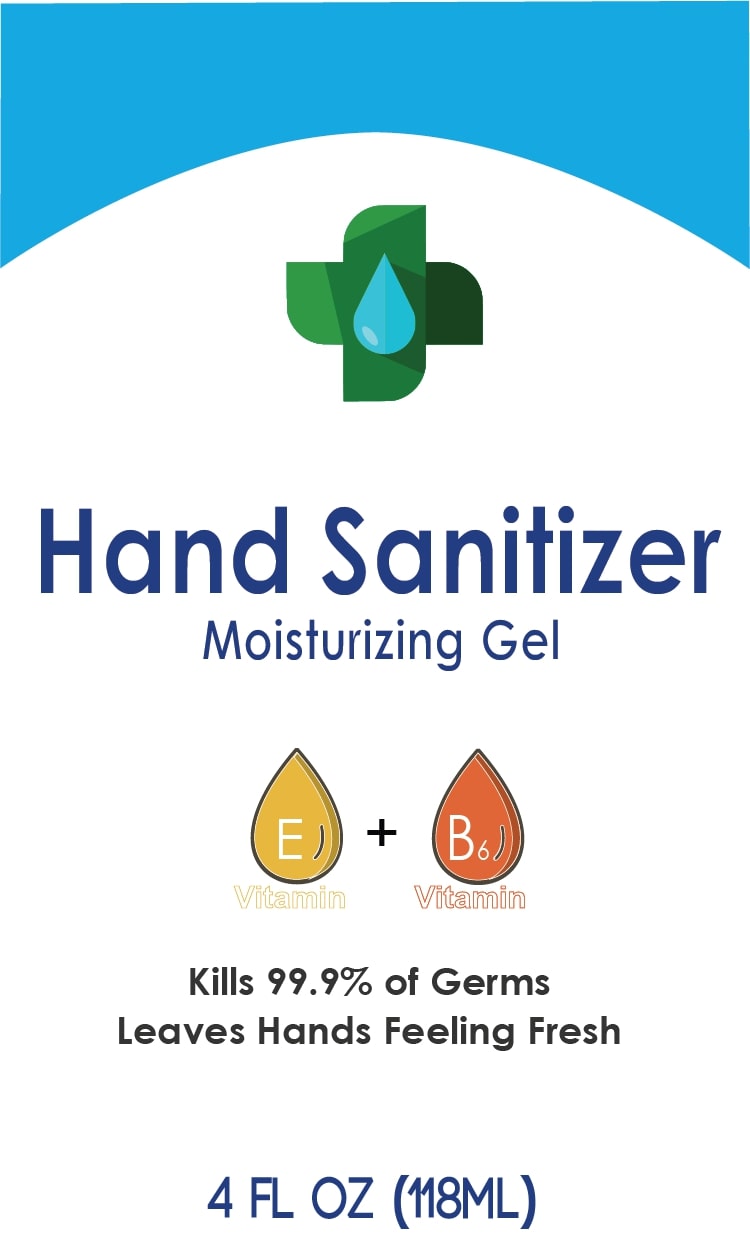 DRUG LABEL: Gel Hand Sanitizer
NDC: 75396-315 | Form: GEL
Manufacturer: BuckAirways Inc.
Category: otc | Type: HUMAN OTC DRUG LABEL
Date: 20200505

ACTIVE INGREDIENTS: ALCOHOL 70 mL/100 mL
INACTIVE INGREDIENTS: .ALPHA.-TOCOPHEROL ACETATE, D-; GLYCERIN; WATER; AMMONIUM ACRYLOYLDIMETHYLTAURATE, DIMETHYLACRYLAMIDE, LAURYL METHACRYLATE AND LAURETH-4 METHACRYLATE COPOLYMER, TRIMETHYLOLPROPANE TRIACRYLATE CROSSLINKED (45000 MPA.S); DEXPANTHENOL

Active Ingredient

Ethyl Alcohol 70% v/v. Purpose: Antiseptic

Purpose

Antiseptic; Hand Sanitizer

Uses

To decrease bacteria on the skin that could cause disease. Reccomended for repeated use. For use when soap and water are not available.

Warnings

For external use only: Hands. Flammable, keep aware from fire or flame.

Do not use

In children less than 2 months of age. On open skin or wounds.

When using this product keep out of eyes, ears, and mouth. In case of contact with eyes, rinse eyes thoroughly with water.

Stop use and ask a doctor ir irritation or rash occurs. These may be signs of a serious condition.

Keep out of reach of children. If swallowed, get medical help or contact a Poison Control Center right away.

Directions

Place enough product on hands to cover all surfaces. Rub hands together until dry.

Supervise children under 6 years of age when using this product to avoid swallowing.

Other information

Store between 15-30C (59-86F)

Avoid freezing and excessive heat above 40C (104F)

Inactive Ingredients

Purified Water USP, Glycerin, Tocopheryl Acetate (Vitamin E), Panthenol (Vitamin B-6), Polyacrylate Crosspolymer-6, Fragerence

Packaging Label - Principal Display Panel

59 ML NDC Code 75396-315-17

FRONT

BACK

118ML NDC Code 75396-315-18

FRONT

BACK

3785ML NDC Code 75396-315-19

FRONT

BACK